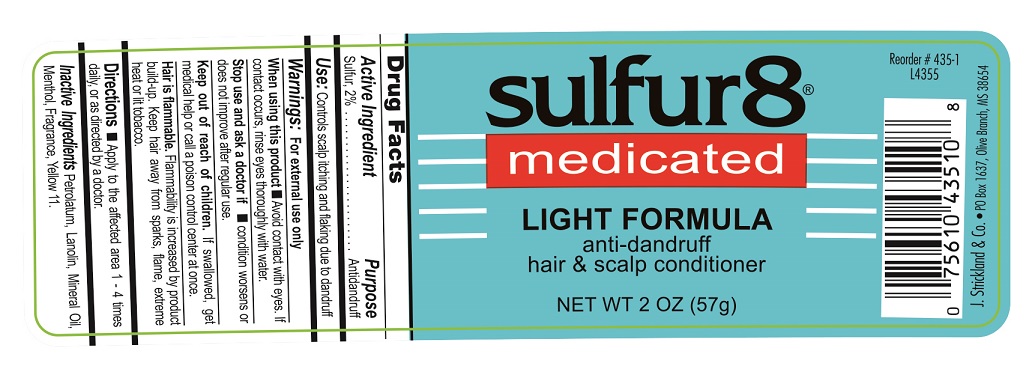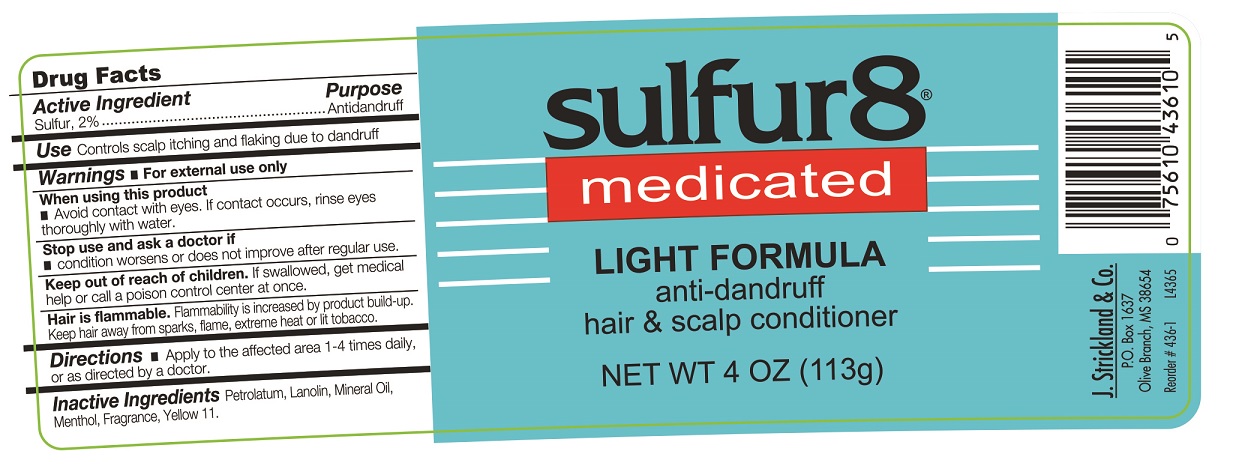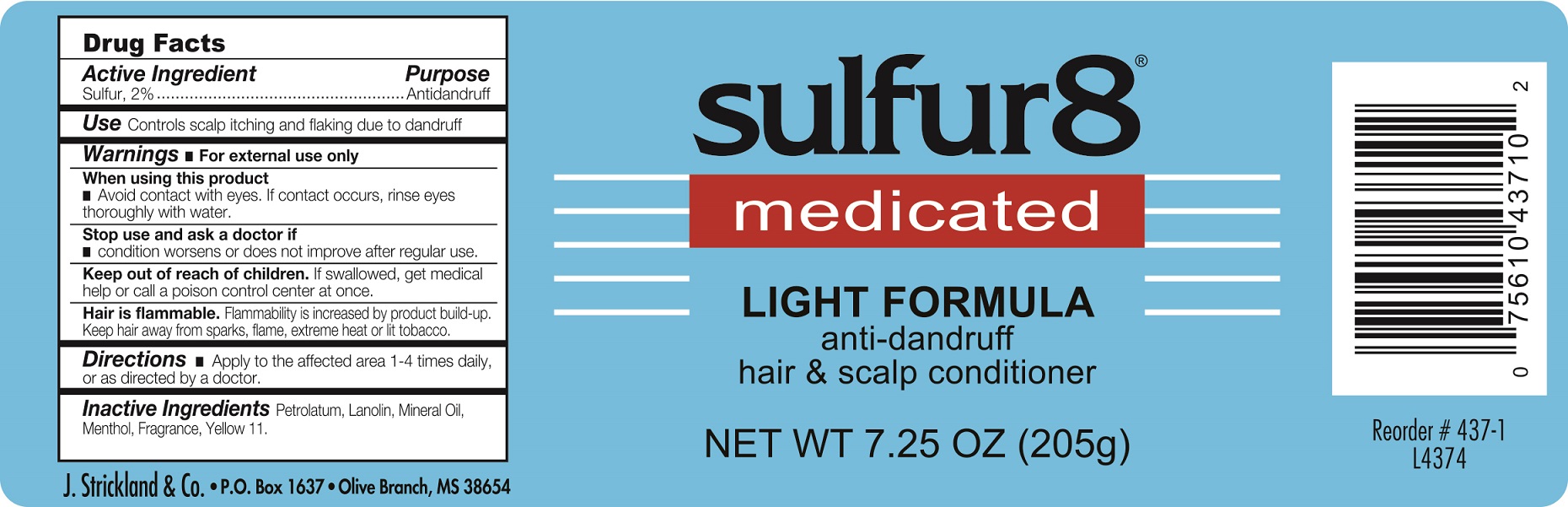 DRUG LABEL: Sulfur 8 Light Anti-Dandruff Hair and Scalp Conditioner
NDC: 12022-018 | Form: OINTMENT
Manufacturer: J. Strickland & Co.
Category: otc | Type: HUMAN OTC DRUG LABEL
Date: 20231021

ACTIVE INGREDIENTS: SULFUR 20 mg/1 g
INACTIVE INGREDIENTS: PETROLATUM; LANOLIN; MINERAL OIL; MENTHOL; D&C YELLOW NO. 11

Sulfur 8 Light Anti-Dandruff Hair and Scalp Conditioner

Active Ingredients

Sulfur, 2%

Purpose

Antidandruff

Use:

Controls scalp itching and flaking due to dandruff

Warnings:

For external use only

When using this product

- do not get into eyes. If contact occurs, rinse eyes thoroughly with water.

Stop use and ask a doctor if

- condition worsens or does not improve after regular use.

If swallowed, get medical help or call a poison control center at once.

- a gradual blue-black darking of the skin occurs
- irritation becomes severe
- no improvement is seen after 3 months

Directions

- Apply to the affected area 1 - 4 times daily, or as directed by a doctor

Inactive Ingredients

Petrolatum, Lanolin, Mineral Oil, Menthol, Fragrance, Yellow 11.